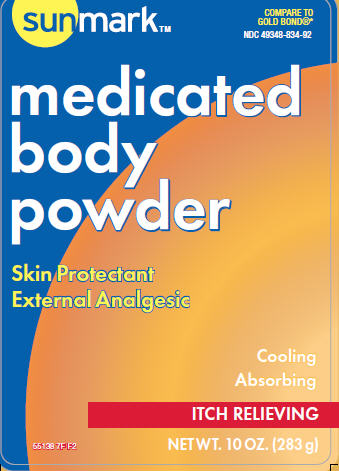 DRUG LABEL: Medicated Body
NDC: 49348-834 | Form: POWDER
Manufacturer: McKesson
Category: otc | Type: HUMAN OTC DRUG LABEL
Date: 20120521

ACTIVE INGREDIENTS: MENTHOL 0.15 g/100 kg; ZINC OXIDE 1.0 g/100 kg
INACTIVE INGREDIENTS: TALC; ACACIA; EUCALYPTOL; METHYL SALICYLATE; SALICYLIC ACID; THYMOL; ZINC STEARATE

Drug Facts

Active ingredients
Menthol 0.15%
Zinc oxide 1.0%

Purpose
External analgesic
Skin protectant

INDICATIONS AND USAGE

Uses for temporary relief of pain and itching due to:
•minor cuts •sunburn •insect bites
•poison ivy •poison oak •poison sumac
•scrapes •minor burns •minor skin irritations
dries the oozing and weeping of:
•poison ivy •poison oak •poison sumac

Warnings
For external use only

When using this product avoid contact with the eyes

Stop use and ask a doctor if condition worsens, or if symptoms persist for more than 7 days or clear up
and occur again within a few days.

Keep out of reach of children. If swallowed, get medical help or contact a Poison Control Center right away

Directions
adults and children 2 years of age and older - apply to affected area not more than 3 to 4 times daily
children under 2 years of age - do not use, consult a doctor
•for best results dry skin thoroughly before applying

INACTIVE INGREDIENT

Inactive ingredients talc, acacia, eucalyptol, methyl salicylate, salicylic acid, thymol, zinc stearate,

This product is not manufactured or distributed by Chattem, Inc., distributor of Gold Bond Medicated Body Powder.
This product is sold by weight, not volume. Some settling may occur during handling and shippint

ADVERSE REACTIONS

Another Quality Product
Distributed By McKesson
One Post Street
San Francisco, CA 94104
Money Back Guarantee
Please visit us at
www.sunmarkbrand.com

PACKAGE LABEL

Sunmark
Compare to
Gold Bond
Medicated
Body
Powder
Skin Protectant
External Analgesic
Cooling
Absorbing
Itch Relieving
NET WT 10 OZ (283 g)